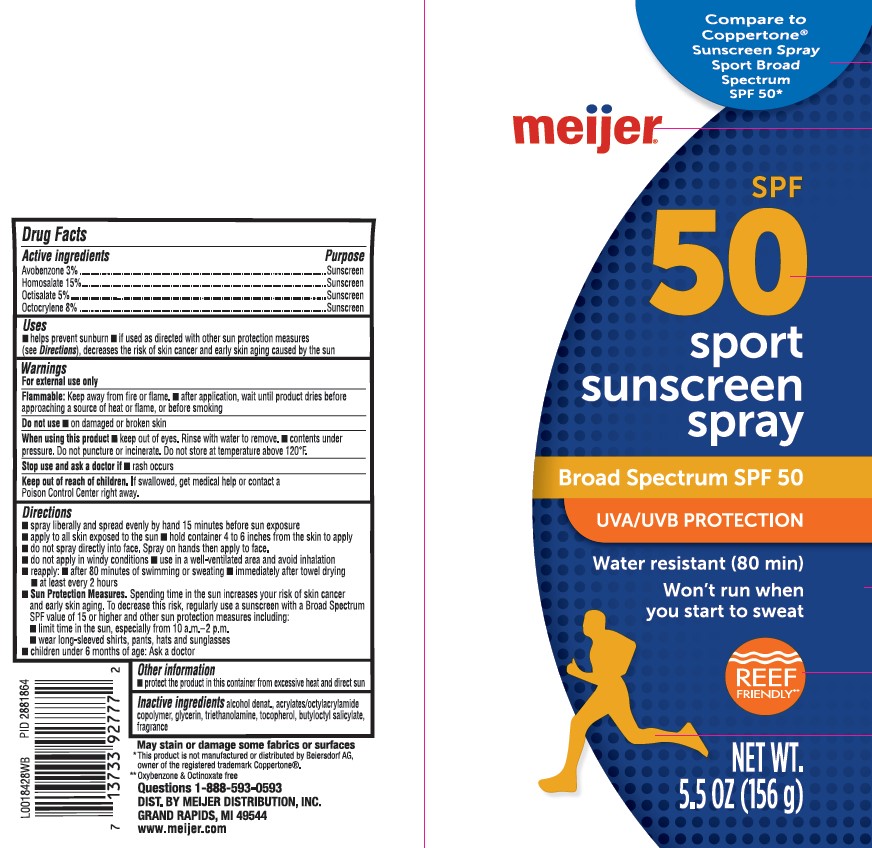 DRUG LABEL: sunscreen
NDC: 79481-0938 | Form: SPRAY
Manufacturer: Meijer, Inc.
Category: otc | Type: HUMAN OTC DRUG LABEL
Date: 20260224

ACTIVE INGREDIENTS: AVOBENZONE 30 mg/1 g; HOMOSALATE 150 mg/1 g; OCTISALATE 50 mg/1 g; OCTOCRYLENE 80 mg/1 g
INACTIVE INGREDIENTS: ALCOHOL; STEAROXYTRIMETHYLSILANE; GLYCERIN; TROLAMINE; TOCOPHEROL; BUTYLOCTYL SALICYLATE

Meijer 938.002/938AB
Sport Sunscreen Spray SPF 50

Active ingredients

Avobenzone 3%

Homosalate 15%

Octisalate 5%

Octocrylene 8%

purpose

sunscreen

uses

- helps prevent sunburn
- if used as directed with other sun protection measures (see Directions), decreases the risk of skin cancer and early skin aging caused by the sun

warnings

For external use only

Flammable

Keep away from fire or flame.

- after application, wait until product dries before approaching a source of heat or flame, or before smoking

do not use

- on damaged or broken skin

When using this product

- keep out of eyes. Rinse with water to remove.
- contents under pressure. Do not puncture or incinerate. Do not store at temperature above 120ºF.

Stop use and ask a doctor if

- rash occurs

Keep out of reach of children.

If swallowed, get medical help or contact a Poison Conrol Center right away.

Directions

■ spray liberally and spread evenly by hand 15 minutes before sun exposure
■ apply to all skin exposed to the sun
■ hold container 4 to 6 inches from the skin to apply
■ do not spray directly into face. Spray on hands then apply to face.
■ do not apply in windy conditions
■ use in a well-ventilated area and avoid inhalation
■ reapply:
■ after 80 minutes of swimming or sweating
■ immediately after towel drying
■ at least every 2 hours
■ Sun Protection Measures. Spending time in the sun increases your risk of skin cancer and early skin aging. To decrease this risk, regularly use a sunscreen with a Broad Spectrum SPF value of 15 or higher and other sun protection measures including:
■ limit time in the sun, especially from 10 a.m.–2 p.m.
■ wear long-sleeved shirts, pants, hats and sunglasses
■ children under 6 months of age: Ask a doctor

other information

- protect the product in the container from excessive heat and direct sun

inactive ingredients

alcohol denat., acrylates/octylacrylamide copolymer, glycerin, triethanolamine, tocopherol, butyloctyl salicylate, fragrance

Disclaimers

May stain or damage some fabrics of surfaces

*This product is not manufactured or distributed by Beiersdorf AG, owner of the registered trademark Coppertone.

**Oxybenzone & Octinoxate free

ADVERSE REACTION

Questions 1-888-593-0593

DIST. BY MEIJER DISTRIBUTION, INC.

GRAND RAPIDS, MI 49544

www.meijer.com

principal display panel

Compare to Coppertone®Sunscreen Spray Sport Broad Spectrum SPF 50*

meijer®

SPF 50

sport

sunscreen

spray

Broad Spectrum SPF 50

UVA/UVB PROTECTION

Water resistant (80 min)

Won't run we you start to sweat

REEF FRIENDLY**

NET WT. 5.5 OZ (156 g)